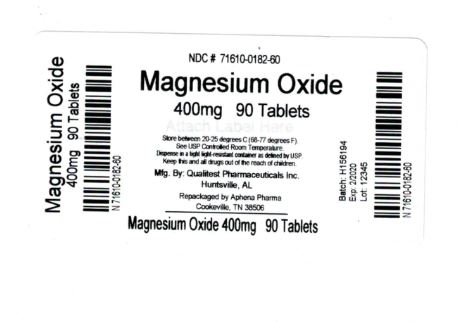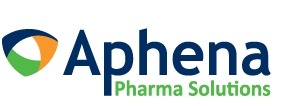 DRUG LABEL: Magnesium Oxide
NDC: 71610-182 | Form: TABLET
Manufacturer: Aphena Pharma Solutions - Tennessee, LLC
Category: otc | Type: HUMAN OTC DRUG LABEL
Date: 20181107

ACTIVE INGREDIENTS: MAGNESIUM OXIDE 400 mg/1 1
INACTIVE INGREDIENTS: SILICON DIOXIDE; CROSCARMELLOSE SODIUM; CELLULOSE, MICROCRYSTALLINE; STEARIC ACID

Magnesium Oxide Tablets

ACTIVE INGREDIENT (In each tablet)

Magnesium Oxide 400mg (241.3mg elemental magnesium)

Purpose

Antacid

USES

Relieves: ■ acid indigestion ■ upset stomach

WARNINGS

Ask a doctor if you have:

kidney disease

Ask a doctor or pharmacist before use if you are:

taking a prescription drug. Antacids may interact with certain prescription drugs.

Do not take

more than 2 tablets in a 24 hour period or use the maximum dosage of this product for more than two weeks, except under the advise and supervision of a physician. May have a laxative effect.

If pregnant or breast-feeding,

ask a health professional before use.

DIRECTIONS

Antacid Directions: ■ take 1 tablet twice a day or as directed by a physician

Magnesium Supplement Directions: ■ take 1 to 2 tablets daily or as directed by a physician

OTHER INFORMATION

■ store at room temperature 59°-86° F (15°-30°C) ■ do not use if imprinted safety seal under cap is broken or missing

■ Magnesium content per tablet: 240 mg

INACTIVE INGREDIENTS

colloidal silicon dioxide, croscarmellose sodium, microcrystalline cellulose, stearic acid

Repackaging Information

Please reference the How Supplied section listed above for a description of individual tablets. This drug product has been received by Aphena Pharma - TN in a manufacturer or distributor packaged configuration and repackaged in full compliance with all applicable cGMP regulations. The package configurations available from Aphena are listed below:

Count | 400 mg
90 | 71610-182-60

Store between 20°-25°C (68°-77°F). See USP Controlled Room Temperature. Dispense in a tight light-resistant container as defined by USP. Keep this and all drugs out of the reach of children.

Repackaged by:
Cookeville, TN 38506
20181107JH

PRINCIPAL DISPLAY PANEL - 400 mg

NDC 71610-182 - Magnesium Oxide 400 mg - Rx Only